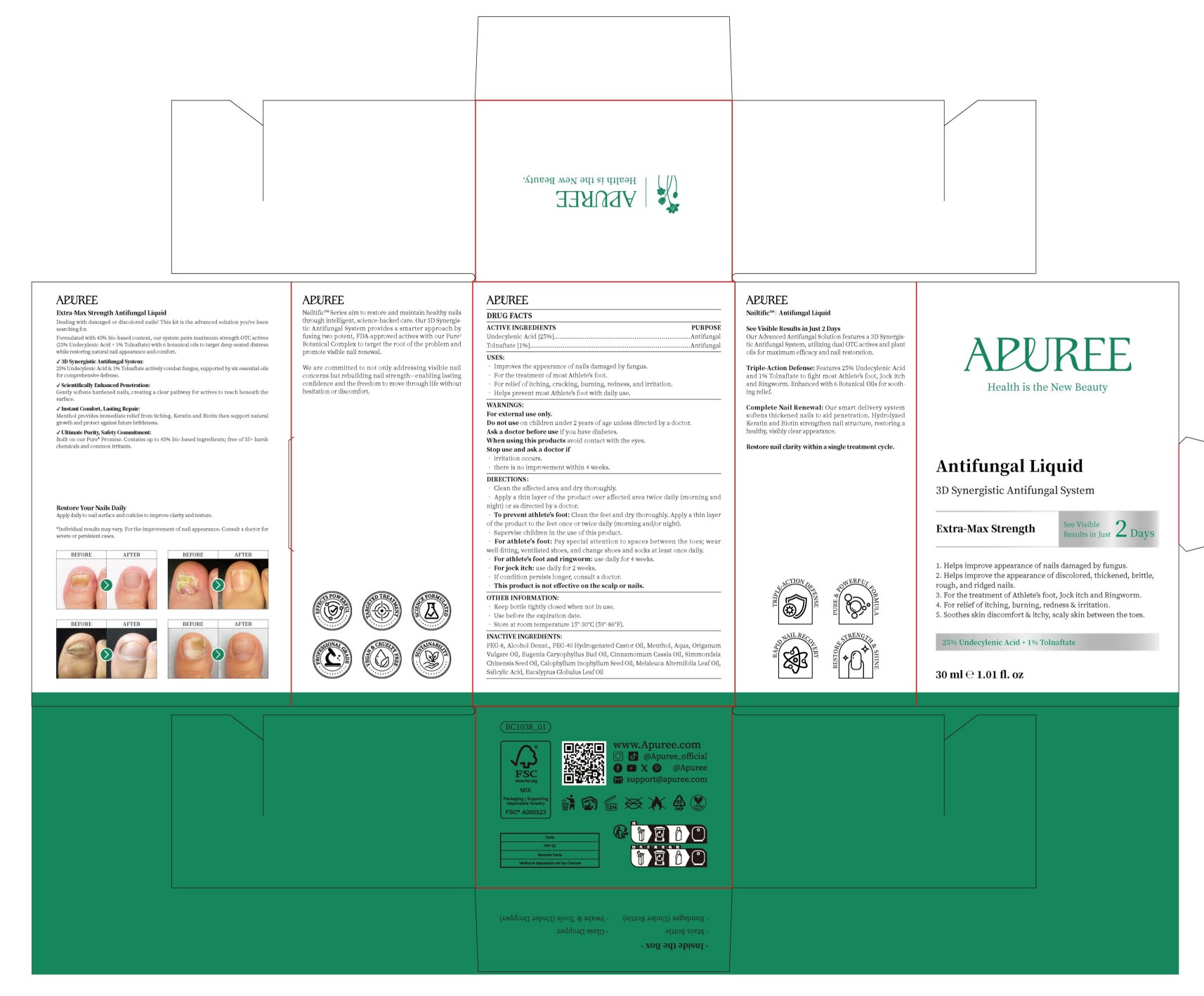 DRUG LABEL: APUREE  Nailtific Extra-Max Strength Antigungal
NDC: 84167-662 | Form: LIQUID
Manufacturer: Guangzhou Meixi Biotechnology Co., Ltd.
Category: otc | Type: HUMAN OTC DRUG LABEL
Date: 20260209

ACTIVE INGREDIENTS: UNDECYLENIC ACID 0.25 g/1 1; TOLNAFTATE 0.01 g/1 1
INACTIVE INGREDIENTS: SIMMONDSIA CHINENSIS (JOJOBA) SEED OIL; CALOPHYLLUM INOPHYLLUM SEED OIL; MELALEUCA ALTERNIFOLIA (TEA TREE) LEAF OIL; DEHYDRATED ALCOHOL; PEG-40 HYDROGENATED CASTOR OIL; EUGENIA CARYOPHYLLUS (CLOVE) BUD OIL; EUCALYPTUS GLOBULUS LEAF OIL; ORIGANUM VULGARE LEAF; AQUA; PEG-8; MENTHOL; CINNAMOMUM CASSIA BARK OIL; SALICYLIC ACID

ACTIVE INGREDIENT

Undecylenic Acid,Tolnaftate

PURPOSE

Sterilization

keep out of reach of children

INDICATIONS AND USAGE

Sterilization

WARNINGS

keep out of reach children

DOSAGE AND ADMINISTRATION

30 ml ℮ 1.01 fl. oz

INACTIVE INGREDIENT

PEG-8,Alcohol Denat,PEG-40 Hydrogenated Castor Oil,Menthol,Aqua,Origanum Vulgare Oil,Eugenia Caryophyllus Bud Oil,
Cinnamomum Cassia Oil,Simmondsia Chinensis Seed Oil,Calophyllum Inophyllum Seed Oil,Melaleuca Alternifolia Leaf Oil,
Salicylic Acid,Eucalyptus Globulus Leaf Oil